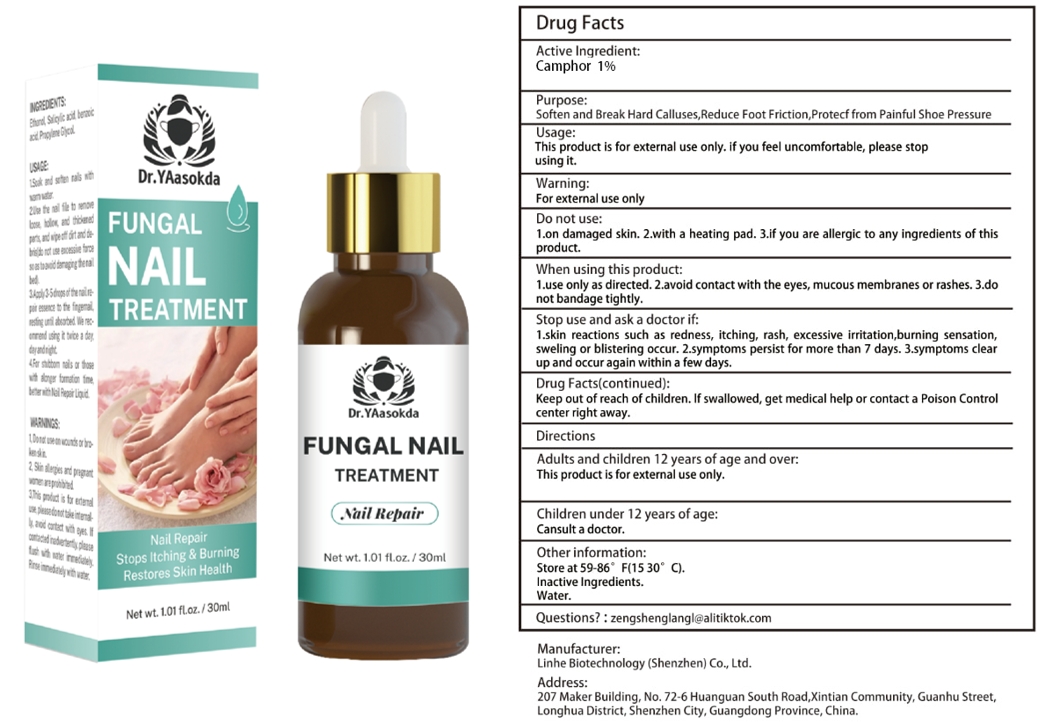 DRUG LABEL: FUNGAL NAIL TREATMENT
NDC: 84575-068 | Form: LIQUID
Manufacturer: Linhe Biotechnology (Shenzhen) Co., Ltd
Category: otc | Type: HUMAN OTC DRUG LABEL
Date: 20241206

ACTIVE INGREDIENTS: CAMPHOR, (-)- 0.3 g/30 mL
INACTIVE INGREDIENTS: GLYCERIN

FUNGAL NAIL TREATMENT

ACTIVE INGREDIENT

CAMPHOR 1%

PURPOSE

Nourish & Moisturise

INDICATIONS AND USAGE

Twist or snip off the capsule neck to open, Squeeze the serum onto your fingertips, Distribute the serum to your hair, from mid-length to the ends

WARNINGS

For external use only.
Patients with renal failure and those with low heart rates should not use this product. This product is notintended to diagnose,treat, cure or prevent any disease.

DOSAGE AND ADMINISTRATION

Take this product and spray it on the glans and coronal sulcus. Spray 1-2 times each time to avoid the urethral opening.

INACTIVE INGREDIENT

WATER

STORAGE AND HANDLING

Store in a cool and dark place away from light

Keep out of reach of children,in case of overdose, get medical help or contact a PoisonControl Center right away.